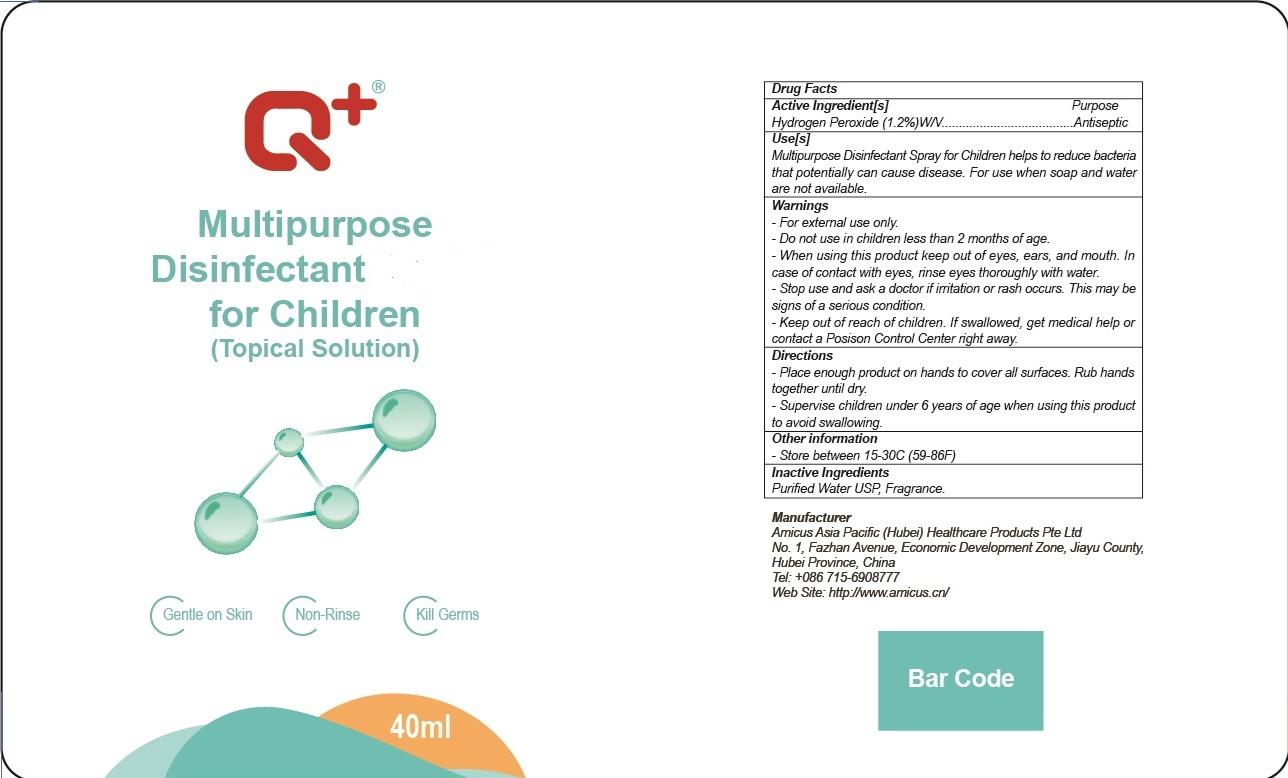 DRUG LABEL: Multipurpose Disinfectant
NDC: 54345-001 | Form: SPRAY
Manufacturer: Amicus Asia Pacific(Hubei) Healthcare Products Pte Ltd
Category: otc | Type: HUMAN OTC DRUG LABEL
Date: 20200703

ACTIVE INGREDIENTS: HYDROGEN PEROXIDE 0.48 g/40 mL
INACTIVE INGREDIENTS: FRAGRANCE LAVENDER & CHIA F-153480; WATER

DOSAGE AND ADMINISTRATION

Store between 15-30°C (59-86°F)

INACTIVE INGREDIENT

Purified Water USP, Fragrance

INDICATIONS AND USAGE

Place enough product on hands to cover all surfaces. Rub hands together until dry.

ACTIVE INGREDIENT

Hydrogen peroxide

keep out of reach of children

PURPOSE

Disinfection
Sterilization
No Rinseing

WARNINGS

For externa/ use only.Do not use in children less than 2 months of age.When using this product keep out of eyes, ears, and mouth. In
case of contact with eyes, rinse eyes thoroughly with water.